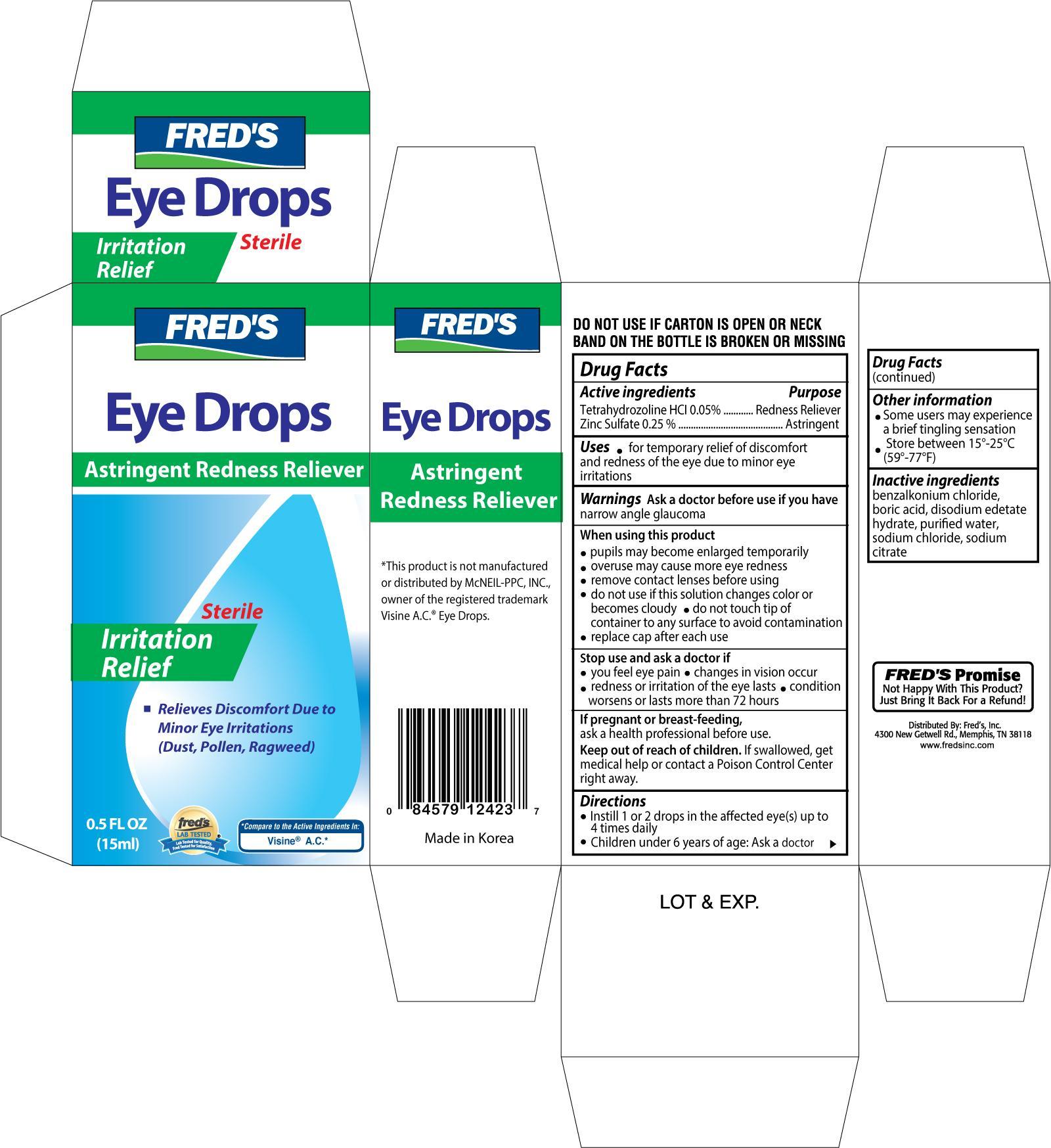 DRUG LABEL: Freds Astringent Rdeness Reliever Eye
NDC: 55315-124 | Form: SOLUTION
Manufacturer: Freds Inc
Category: otc | Type: HUMAN OTC DRUG LABEL
Date: 20130630

ACTIVE INGREDIENTS: TETRAHYDROZOLINE HYDROCHLORIDE 0.05 mg/1 mg; ZINC SULFATE 0.25 mg/1 mg
INACTIVE INGREDIENTS: BENZALKONIUM CHLORIDE; BORIC ACID; WATER; SODIUM CHLORIDE; SODIUM CITRATE

Drug Facts

Active ingredients Purpose

Tetrahydrozoline HCl 0.05%......................................................Redness Reliever

Zinc Sulfate 0.25%..............................................................................Astringent

Uses

- For temporary relief of discomfort and redness of the eye due to minor eye irritations

Warnings for external use only

Ask a doctor before use if you have narrow angle glaucoma

When using this product

- pupils may become enlarged temporarily
- overuse may cause more eye redness
- remove contact lenses before using
- do not use if this solution changes color or becomes cloudy
- do not touch tips of container to any surface to avoid contamination
- replace cap after each use

Stop use and ask a doctor if

- you feel eye pain
- changes in vision occur
- redness or irritation of they eye lasts
- condition worsens or lasts more than 72 hours

PREGNANCY OR BREAST FEEDING

If pregnant or breast feeding, ask a health professional before use.

Keep out of reach of children. If swallowed, get medical help or contact a Poison Control Center right away.

Directions

- Instill 1 or 2 drops in the affected eye(s) up to 4 times daily
- Children under 6 years of age: Ask a doctor

Other information

- some users may experience a brief tingling sensation
- store between 15°-25°C (59°-77°F)

INACTIVE INGREDIENT

Inactive ingredients benzalkonium chloride, boric acid, disodium edetate hydrate, purified water, sodium chloride, sodium citrate

DOSAGE AND ADMINISTRATION

Distributed By:

Fred's Inc.

4300 New Getwell Rd.

Memphis, TN 38118

Made in Korea